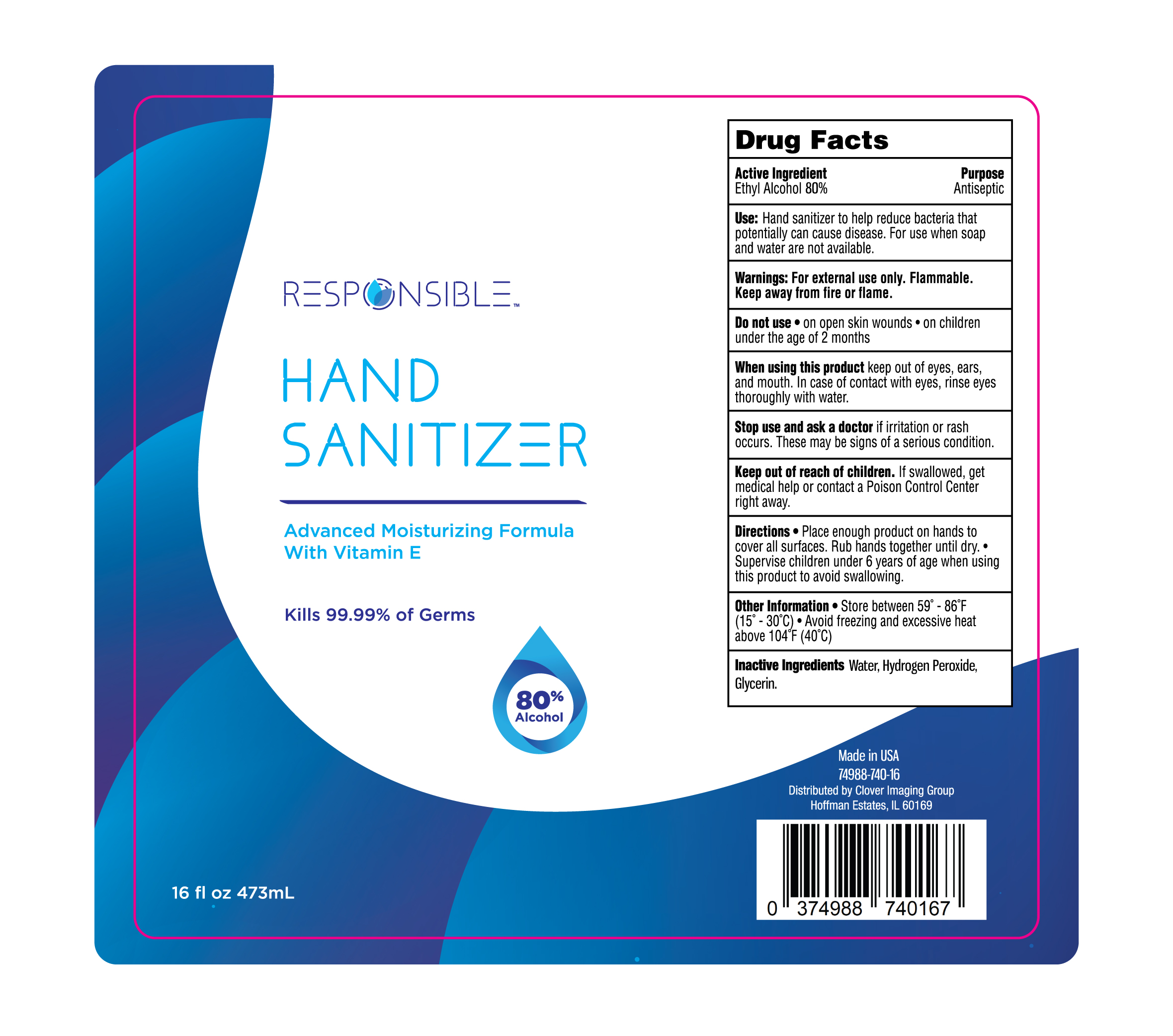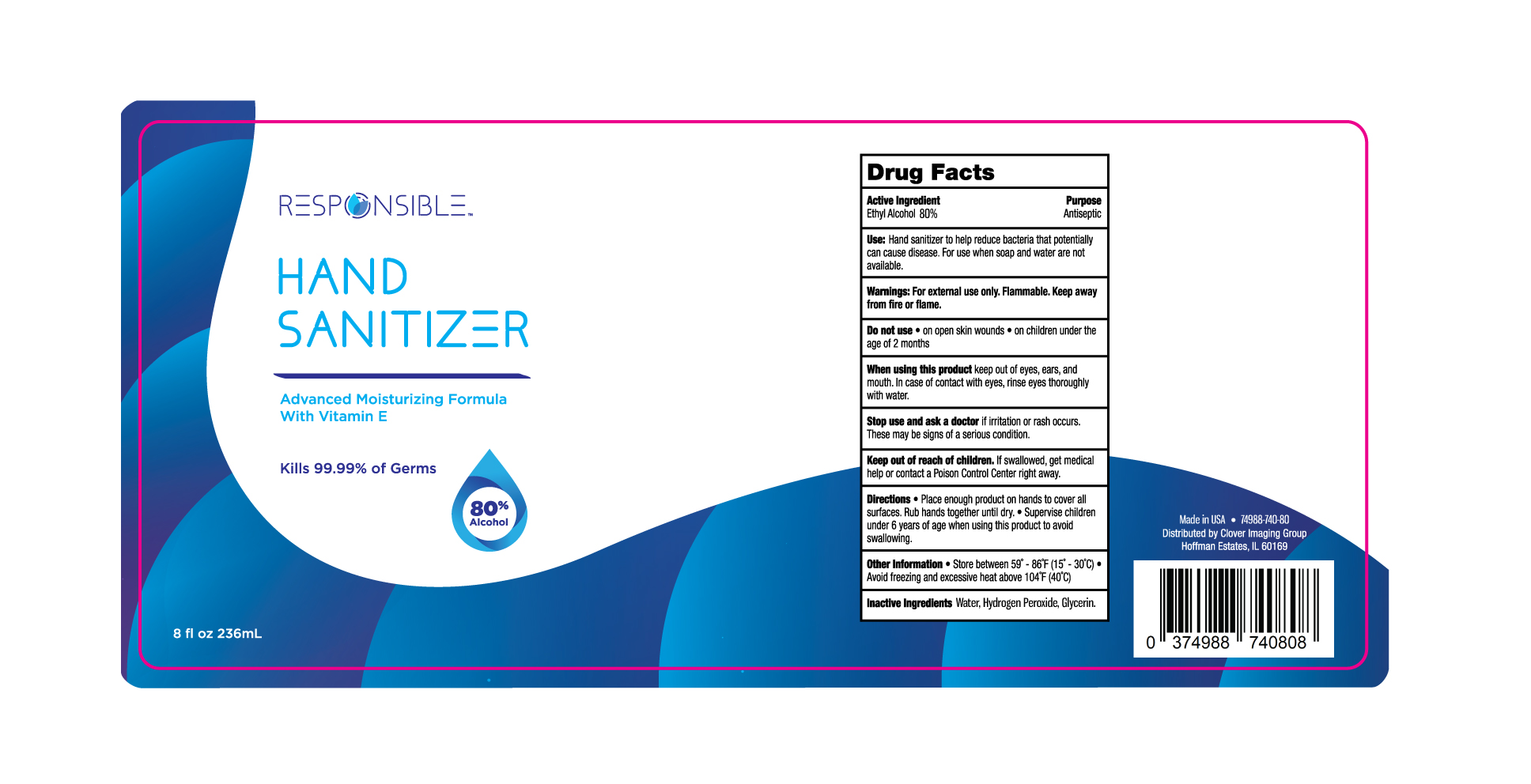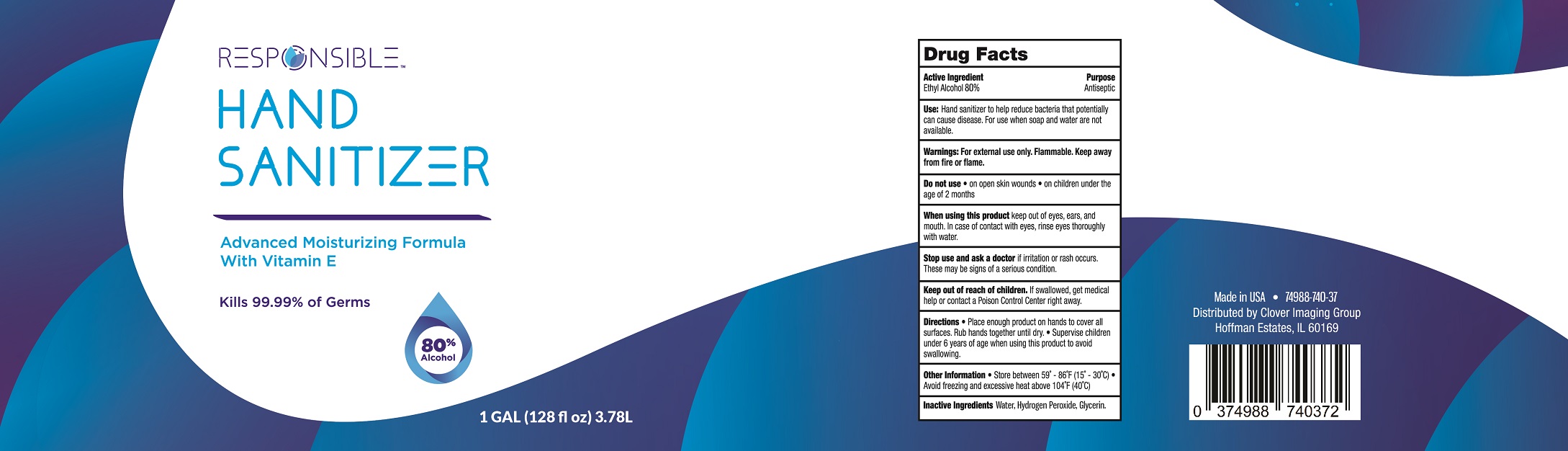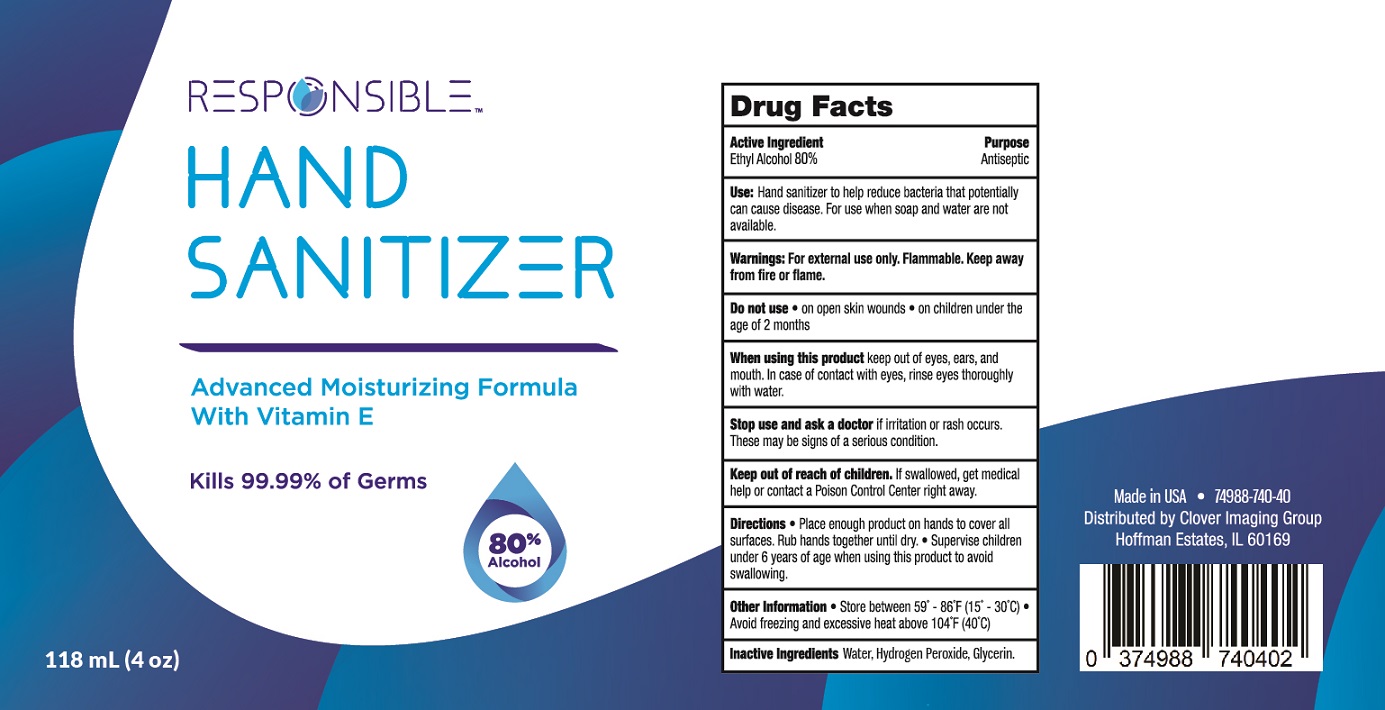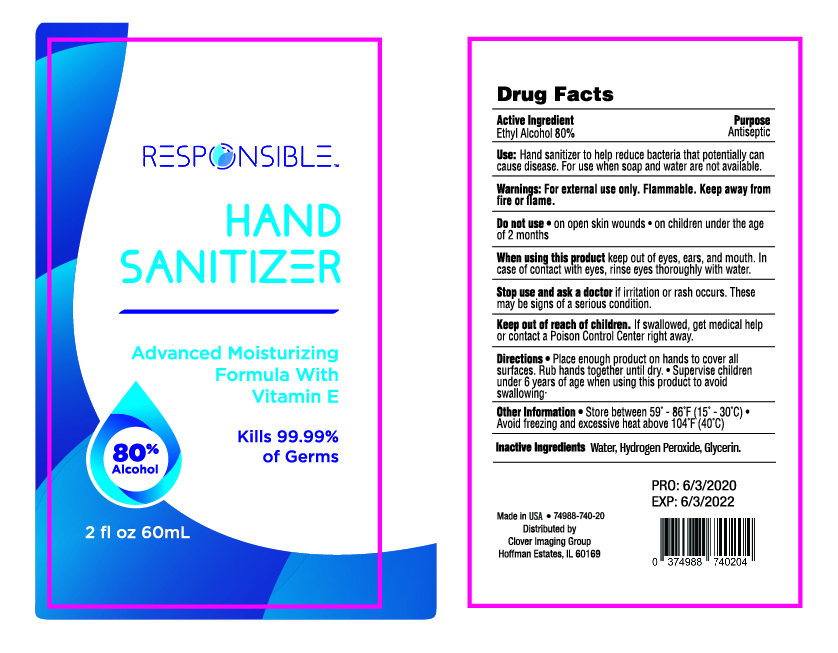 DRUG LABEL: Responsible Hand Sanitizer
NDC: 74988-740 | Form: LIQUID
Manufacturer: SanitizeNow Inc.
Category: otc | Type: HUMAN OTC DRUG LABEL
Date: 20210106

ACTIVE INGREDIENTS: ALCOHOL 80 mL/100 mL
INACTIVE INGREDIENTS: GLYCERIN 1.45 mL/100 mL; HYDROGEN PEROXIDE 0.125 mL/100 mL; WATER

Disclaimer: Most OTC drugs are not reviewed and approved by FDA, however they may be marketed if they comply with applicable regulations and policies. FDA has not evaluated whether this product complies.

The hand sanitizer is manufactured using only the following ingredients in the preparation of the product:

Alcohol (ethanol) (80%, volume/volume (v/v)) in an aqueous solution denatured according to Alcohol and Tobacco Tax and Trade Bureau regulations in 27 CFR part 20.
Sterile distilled water or boiled cold water.
Hydrogen Peroxide
Glycerin

The firm does not add other active or inactive ingredients. Different or additional ingredients may impact the quality and potency of the product.

Active Ingredient(s)

Alcohol 80% v/v. Purpose: Antiseptic

Purpose

Antiseptic, Hand Sanitizer

Use

Hand Sanitizer to help reduce bacteria that potentially can cause disease. For use when soap and water are not available.

Warnings

For external use only. Flammable. Keep away from heat or flame

Do not use

- in children less than 2 months of age
- on open skin wounds

When using this product keep out of eyes, ears, and mouth. In case of contact with eyes, rinse eyes thoroughly with water.
Stop use and ask a doctor if irritation or rash occurs. These may be signs of a serious condition.
Keep out of reach of children. If swallowed, get medical help or contact a Poison Control Center right away.

Stop use and ask a doctor if irritation or rash occurs. These may be signs of a serious condition.

Keep out of reach of children. If swallowed, get medical help or contact a Poison Control Center right away.

Directions

- Place enough product on hands to cover all surfaces. Rub hands together until dry.
- Supervise children under 6 years of age when using this product to avoid swallowing.

Other information

- Store between 15-30C (59-86F)
- Avoid freezing and excessive heat above 40C (104F)

Inactive ingredients

Water, Hydrogen Peroxide, Glycerin.

Package Label - Principal Display Panel

59 mL NDC: 74988-740-20
118 mL NDC: 74988-740-40
236 mL NDC: 74988-740-80
473 mL NDC: 74988-740-16
3.78 L NDC: 74988-740-37